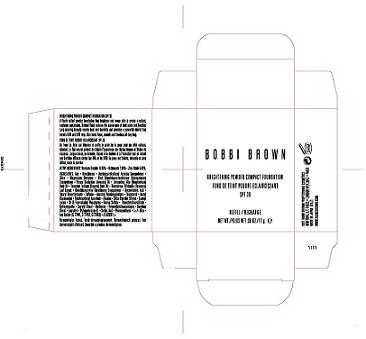 DRUG LABEL: BRIGHTENING POWDER  
NDC: 64141-718 | Form: POWDER
Manufacturer: Bobbi Brown Professional Cosmetics Inc. 
Category: otc | Type: HUMAN OTC DRUG LABEL
Date: 20100406

ACTIVE INGREDIENTS: TITANIUM DIOXIDE 18.6 g/100 g; OCTINOXATE 7.0 g/100 g; ZINC OXIDE 5.8 g/100 g

ACTIVE INGREDIENT

ACTIVE INGREDIENTS: TITANIUM DIOXIDE 18.60% [] OCTINOXATE 7.00% [] ZINC OXIDE 5.80%

PACKAGE LABEL

PRINCIPAL DISPLAY PANEL:

BOBBI BROWN

BRIGHTENING POWDER COMPACT FOUNDATION

SPF 20

REFILL/RECHARGE

NT WT. .38 OZ/ 11 g

DISTR. BOBBI BROWN PROFESSIONAL COSMETICS

NY, NY 10022

E3L7

BOBBI BROWN.COM